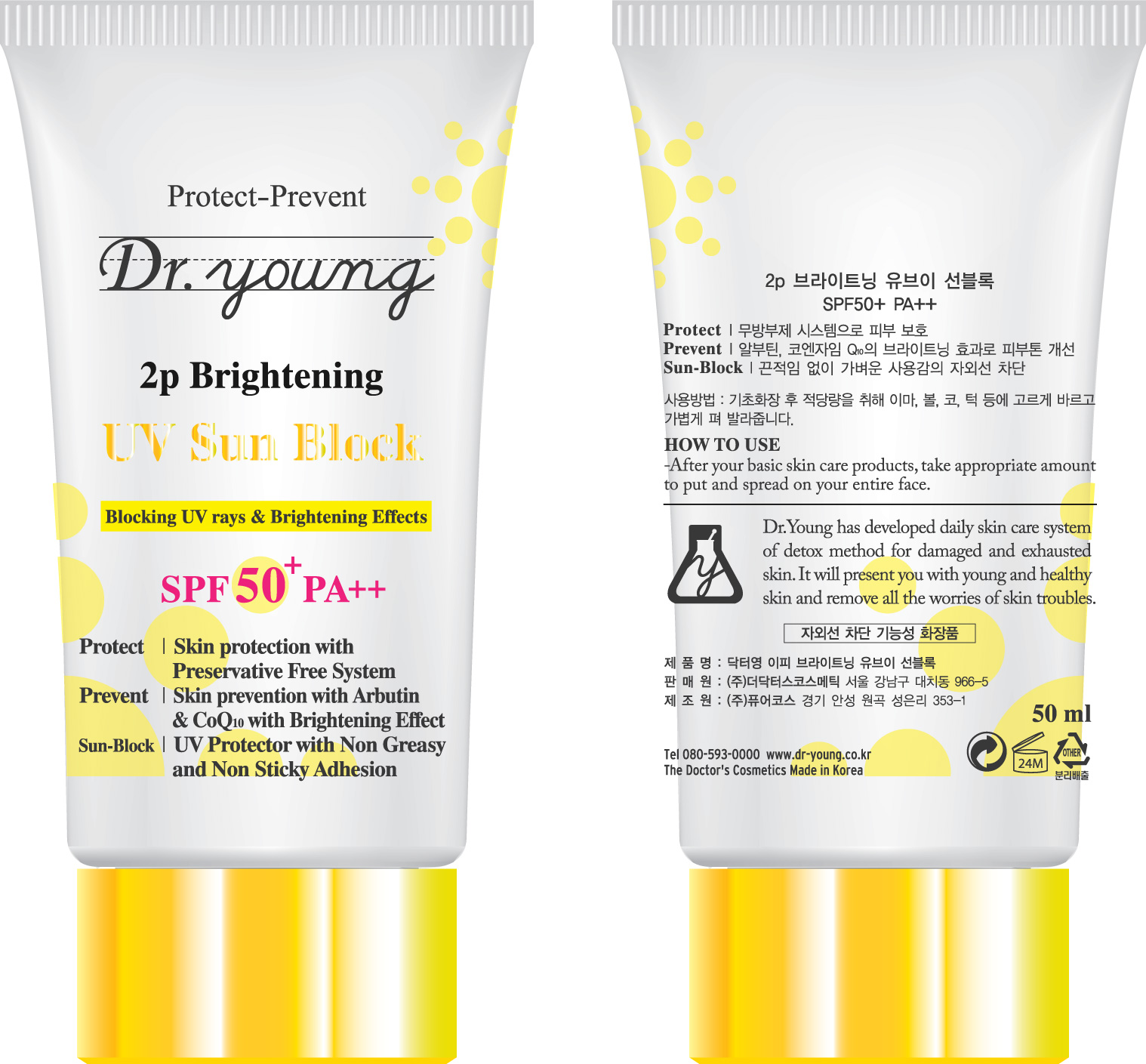 DRUG LABEL: Dr Young 2p Brightening UV Sun Block SPF50 PA
NDC: 43948-5003 | Form: CREAM
Manufacturer: The Doctor's Cosmetic Inc
Category: otc | Type: HUMAN OTC DRUG LABEL
Date: 20091001

ACTIVE INGREDIENTS: ARBUTIN 0.5 mL/50 mL; OCTINOXATE 2.5 mL/50 mL

ACTIVE INGREDIENTS:

Hyaluronic Acid, Scutellaria Baicalensis Root Extract, Beta-Glucan, Phytosterols, Arbutin, Octinoxate

CAUTION: Keep away from children.

WHEN USING

HOW TO USE:

After your basic skin care products, take appropriate amount to put and spread on your entire face.